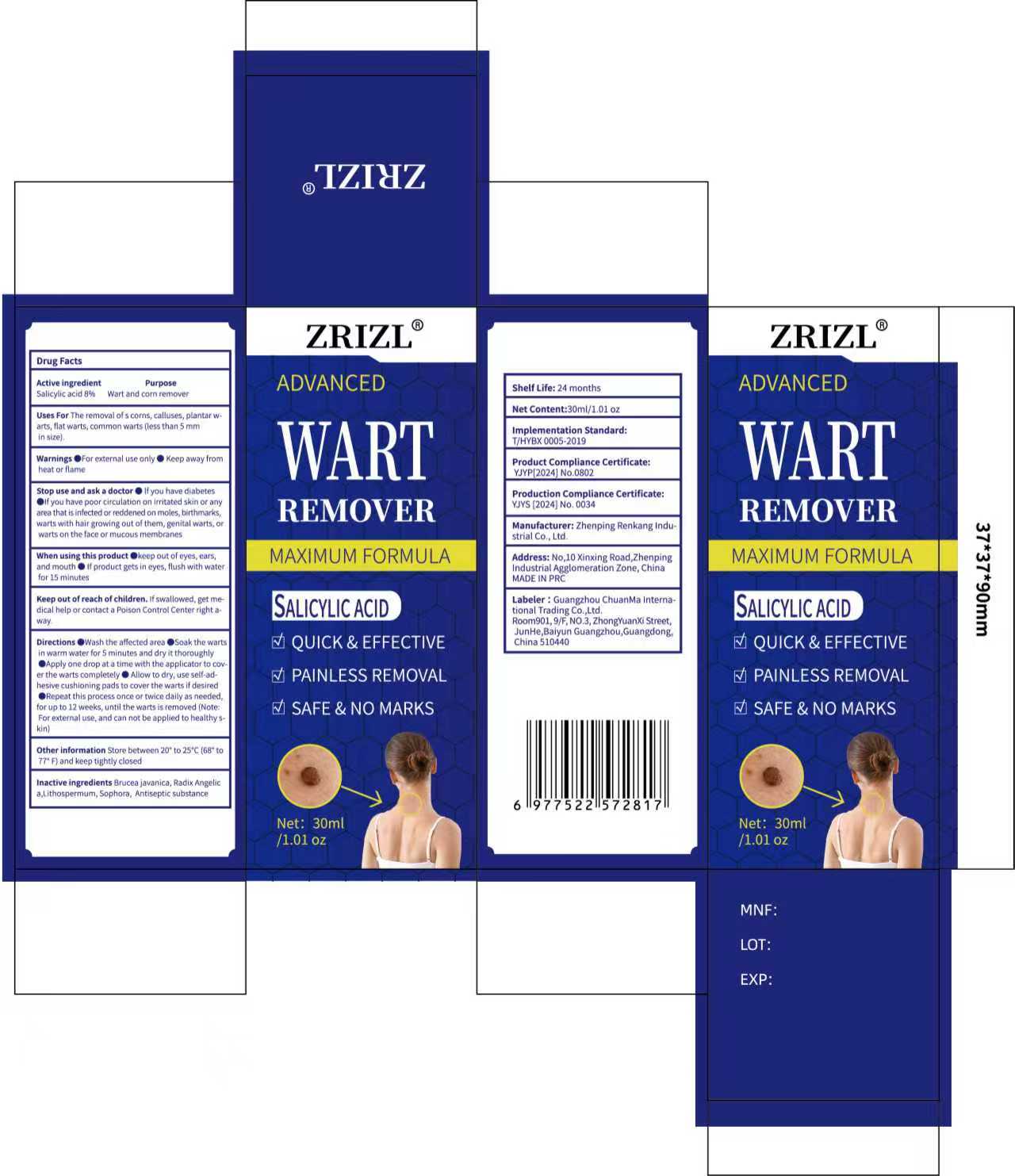 DRUG LABEL: ZRIZL wart Remover
NDC: 85593-015 | Form: LIQUID
Manufacturer: Guangzhou ChuanMa International Trading Co.,Ltd.
Category: otc | Type: HUMAN OTC DRUG LABEL
Date: 20250914

ACTIVE INGREDIENTS: SALICYLIC ACID 8 g/100 mL
INACTIVE INGREDIENTS: ALCOHOL; ANGELICA DAHURICA VAR. FORMOSANA WHOLE; LITHOSPERMUM INCISUM WHOLE; SOPHORA FLAVESCENS ROOT; BRUCEA JAVANICA WHOLE

ACTIVE INGREDIENT

Salicylic acid 8% w/w

PURPOSE

Uses For The removai ol s corns, calluses, piantar warts, filat warts, comman warts (less than 5 mmin stze)

WARNINGS

Warnings o For exernal use only ，Keep away fromheat or flame

KEEP OUT OF REACH OF CHILDREN

Keep out of reach ofchildren, lfswallowed, get medical help or contact a Poison controt center right a-way

DOSAGE AND ADMINISTRATION

Wash the affected area ， Soak the.wartsin warm water for 5 minutes aind dryit thoroughly Apply one drop at a time with the applicator to cov.er the warts completely o Allow to dry, use self adhesive cushloning pads to cover the warts if deslred@Repeat this pracess once or twice dally as neededfor up to 12 weeks, until the warts is removed (Nte.For external use, and can not be applied to healthy skin)

INACTIVE INGREDIENT

ALCOHOL
SOPHORA FLAVESCENS ROOT
LITHOSPERMUM INCISUM WHOLEANGELICA DAHURICA VAR. FORMOSANA WHOLEBRUCEA JAVANICA WHOLE

INDICATIONS AND USAGE

keep out of eyes, ear ;and mouth if product gets in eyes, flush with waterfor 15 minutes